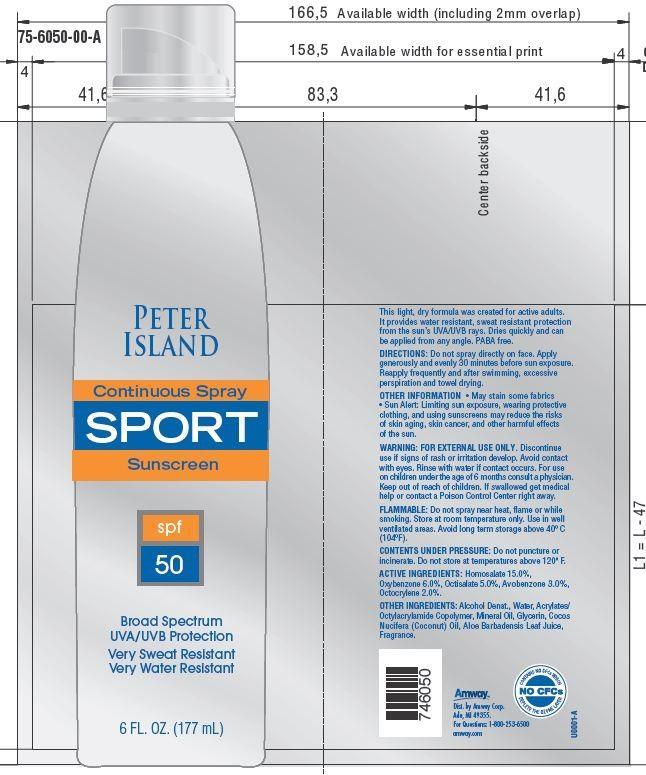 DRUG LABEL: Peter Island Continuous Sport Sunscreen
NDC: 10056-701 | Form: SPRAY
Manufacturer: Access Business Group LLC
Category: otc | Type: HUMAN OTC DRUG LABEL
Date: 20130627

ACTIVE INGREDIENTS: HOMOSALATE 15 g/100 g; OXYBENZONE 6 g/100 g; AVOBENZONE 3 g/100 g; OCTISALATE 5 g/100 g; OCTOCRYLENE 2 g/100 g
INACTIVE INGREDIENTS: WATER; MINERAL OIL; GLYCERIN; COCONUT OIL; ALOE VERA LEAF

ACTIVE INGREDIENTS:

Homosalate 15.0%

Oxybenzone 6.0%

Octisalate 5.0%

Avobenzone 3.0%

Octocrylene 2.0%

WARNING:

FOR EXTERNAL USE ONLY.
Avoid contact with eyes. Rinse with water if contact occurs.

STOP USE

Discontinue use if signs of rash or irritation develop.

ASK DOCTOR

For use on children under the age of 6 months consult a physician.

Keep out of reach of children. If swallowed get medical help or contact a Poison Control Center right away.

FLAMMABLE

Do not spray near heat, flame or while smoking. Store at room temperature only. Use in well ventilated areas. Avoid long term storage above 40o C(104o F).

CONTENTS UNDER PRESSURE: Do not puncture or incinerate.Do not store at temperatures above 120o F.

DIRECTIONS

Do not spray directly on face. Apply generously and evenly 30 minutes before sun exposure. Reapply frequently and after swimming, excessive perspiration and towel drying.

OTHER INFORMATION

- May stain some fabrics
- Sun Alert: Limiting sun exposure, wearing protective clothing, and using sunscreens may reduce the risks of skin aging, skin cancer, and other harmful effects of the sun.

This light, dry formula was created for active adults. It provides water resistant, sweat resistant protection from the sun's UVA/UVB rays. Dries quickly and can be applied from any angle. PABA free.

Principal Display Panel

PETER ISLAND

Continuous Spray SPORT

Sunscreen

spf 50

Broad Spectrum

UVA/UVB Protection

Very Sweat resistant

Very Water Resistant

6 FL.OZ. (177 mL)

OTHER INGREDIENTS:

Alcohol Denat.,Water, Acrylates/Octylacrylamide Copolymer, Mineral Oil, Glycerin,Cocos Nucifera (Coconut) Oil, Aloe Barbadensis Leaf Extract, Fragrance.